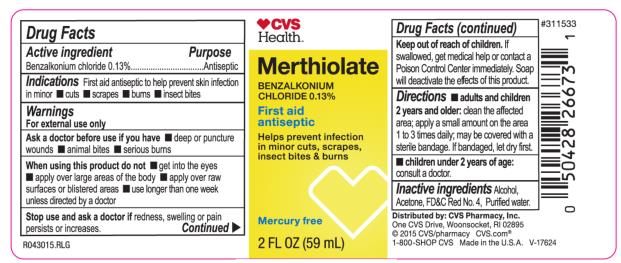 DRUG LABEL: CVS Merthiolate
NDC: 69842-749 | Form: LIQUID
Manufacturer: CVS Pharmacy
Category: otc | Type: HUMAN OTC DRUG LABEL
Date: 20231222

ACTIVE INGREDIENTS: BENZALKONIUM CHLORIDE 1.3 mg/1 mL
INACTIVE INGREDIENTS: ACETONE; FD&C RED NO. 4; WATER

CVS Merthiolate

CVS Merthiolate

Drug Facts

Active Ingredient

Benzalkonium Chloride 0.13%

Purpose

Antiseptic

Indications

First aid antiseptic to help skin infection in minor: cuts, scrapes, burns, insect bites.

Warnings

For external use only.

Ask a doctor before use if you have

Deep or puncture wounds

Animal bites

Serious burns

When using this product do not

Get into the eyes

Apply over large areas of the body

Apply over raw surfaces or blistered areas

Use longer than one week unless directed by doctor.

Stop use and ask a doctor if

- Redness, swelling or pain persists or increases.

Keep out of reach of children.

- If swallowed, get medical help or contact a Poison Control Center immediately. Soap will deactivate the effects of this product.

Directions

- Adults and children 2 years and older. Clean the affected area; apply a small amount on the area 1 to 3 times daily; may be covered with a sterile bandage. If bandaged, let dry first.
- Children under 2 yrs. of age: Consult a doctor.

Inactive Ingredient

Acetone, FD&C Red No 4. Purified water.

PRINCIPAL DISPLAY PANEL

CVS
Merthiolate
Benzalkonium
Chloride 0.13%
Mercury free
2 FL OZ (59 mL)